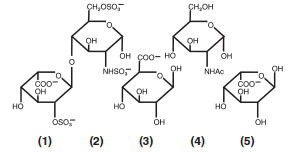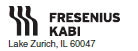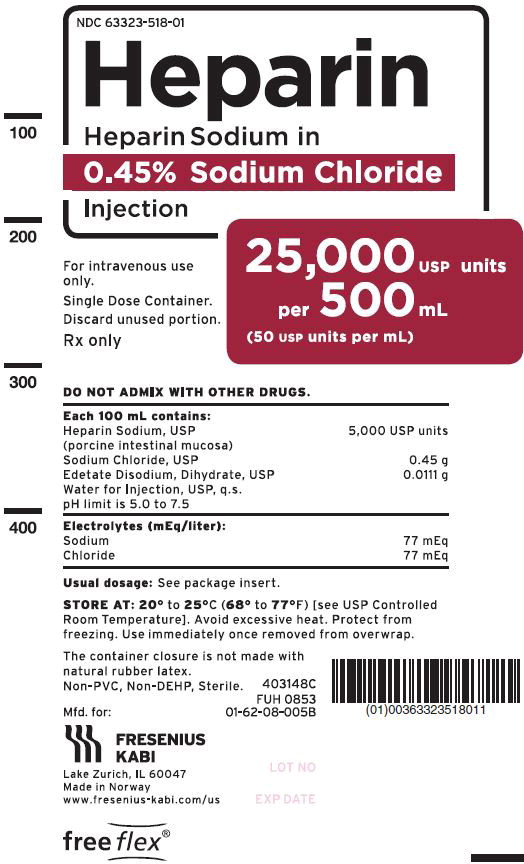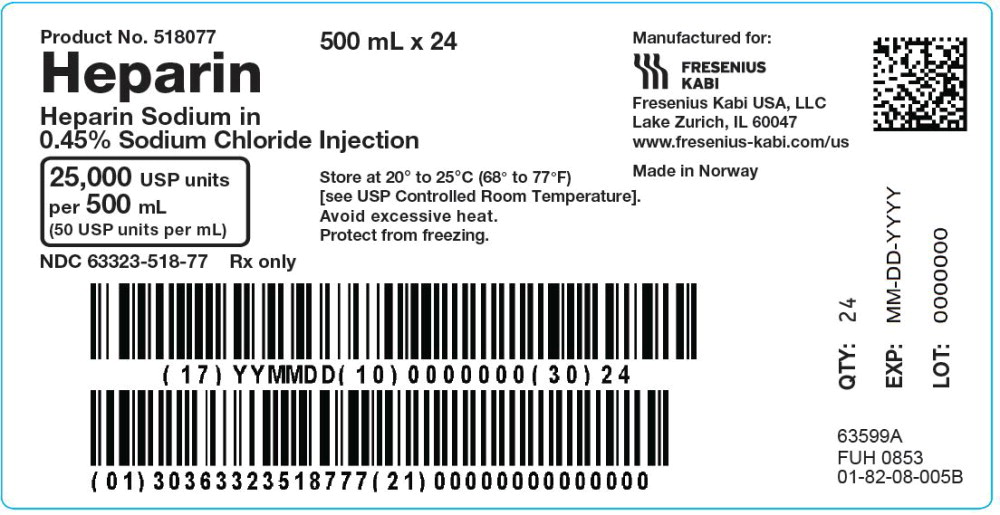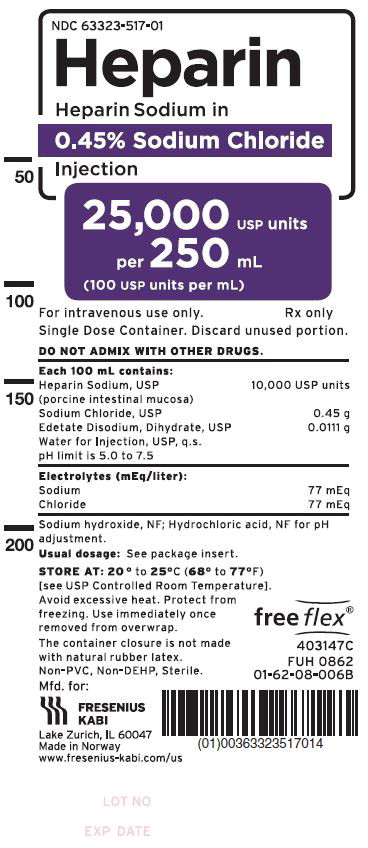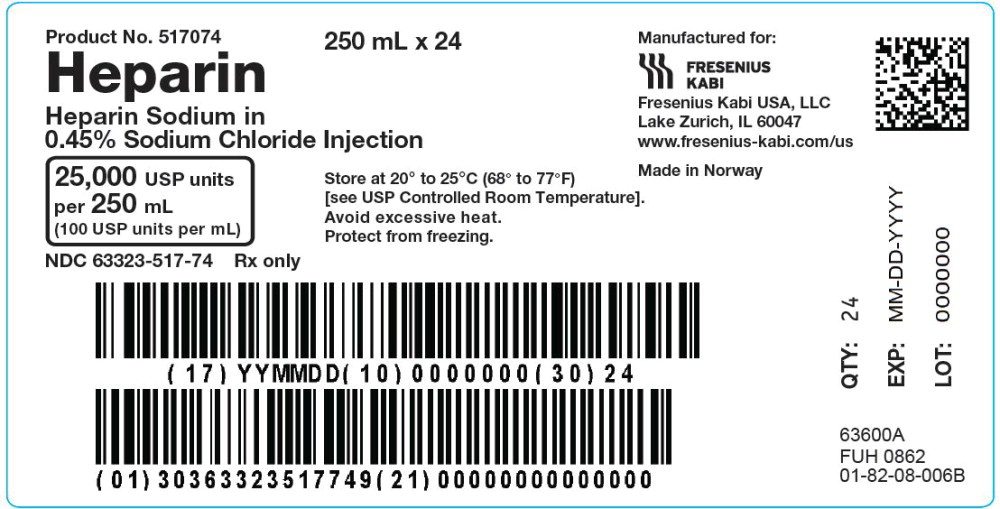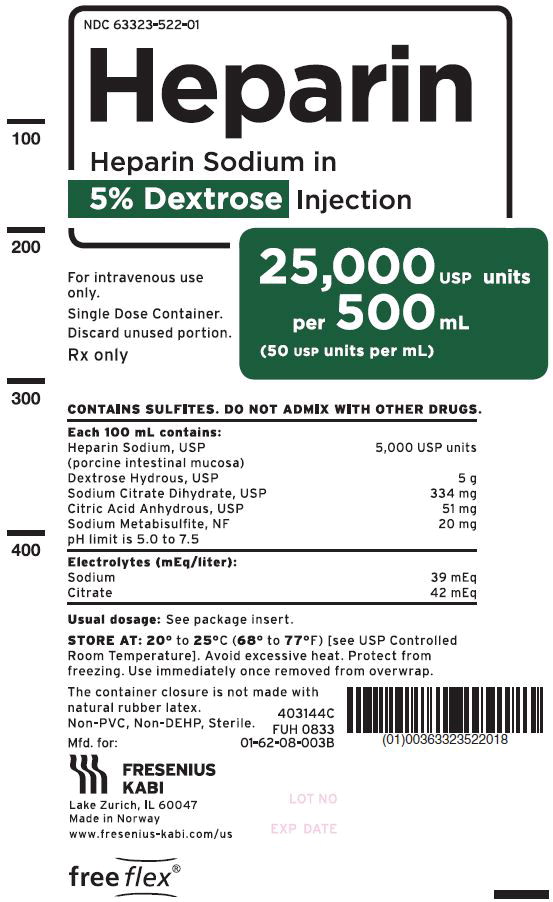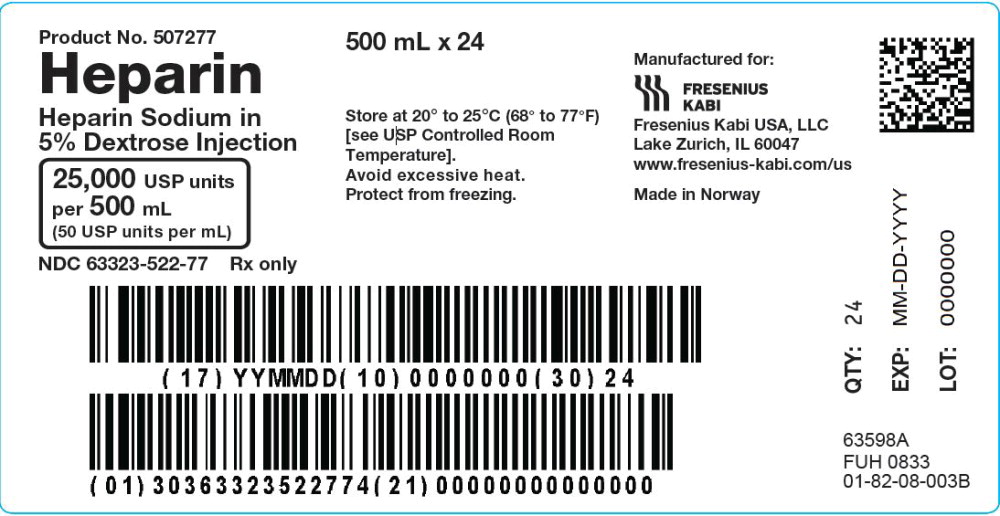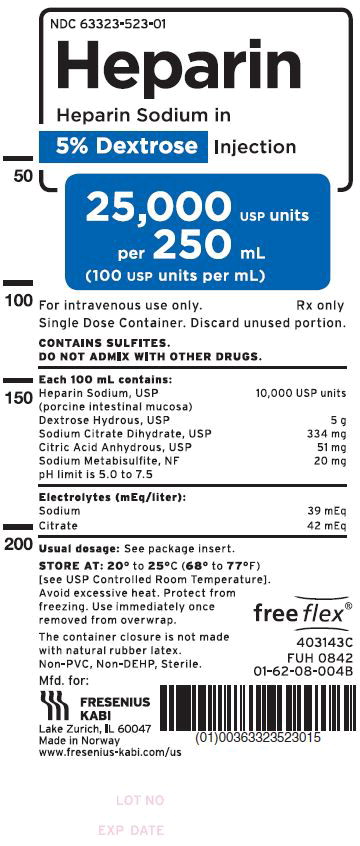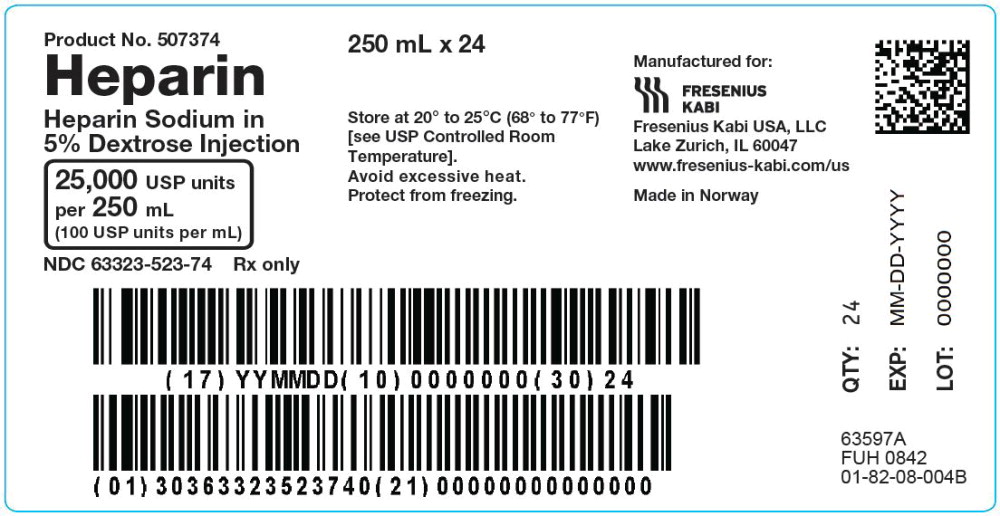 DRUG LABEL: Heparin Sodium

NDC: 63323-522 | Form: INJECTION, SOLUTION
Manufacturer: Fresenius Kabi USA, LLC
Category: prescription | Type: HUMAN PRESCRIPTION DRUG LABEL
Date: 20240430

ACTIVE INGREDIENTS: HEPARIN SODIUM 5000 [USP'U]/100 mL
INACTIVE INGREDIENTS: DEXTROSE MONOHYDRATE; ANHYDROUS CITRIC ACID; TRISODIUM CITRATE DIHYDRATE; SODIUM METABISULFITE

HIGHLIGHTS OF PRESCRIBING INFORMATION

These highlights do not include all the information needed to use HEPARIN SODIUM IN 0.45% SODIUM CHLORIDE INJECTION or HEPARIN SODIUM IN 5% DEXTROSE INJECTION safely and effectively. See full prescribing information for HEPARIN SODIUM IN 0.45% SODIUM CHLORIDE INJECTION or HEPARIN SODIUM IN 5% DEXTROSE INJECTION.
HEPARIN SODIUM, for intravenous use
Initial U.S. Approval: 1939
Rx only

1 INDICATIONS AND USAGE

Heparin sodium is an anticoagulant indicated for: (1)

- Prophylaxis and treatment of venous thromboembolism and pulmonary embolism
- Atrial fibrillation with embolization
- Treatment of acute and chronic consumptive coagulopathies (disseminated intravascular coagulation)
- Prevention of clotting in arterial and cardiac surgery
- Prophylaxis and treatment of peripheral arterial embolism
- Anticoagulant use in blood transfusions, extracorporeal circulation, and dialysis procedures.

2 DOSAGE AND ADMINISTRATION

Recommended Adult Dosages:

- Therapeutic Anticoagulant Effect with Full-Dose Heparin* (2.3)

Intermittent Intravenous Injection | Initial Dose | 10,000 units
Intermittent Intravenous Injection | Every 4 to 6 hours | 5,000 to 10,000 units
Continuous Intravenous Infusion | Initial Dose | 5,000 units by intravenous injection
Continuous Intravenous Infusion | Continuous | 20,000 to 40,000 units/24 hours
*Based on 150 lb. (68 kg) patient.

- Surgery of the Heart and Blood Vessels (2.5)

Intravascular via Total Body Perfusion | Initial Dose | ≥ 150 units/kg; adjust for longer procedures

- Extracorporeal Dialysis (2.8)

Intravascular via Extracorporeal Dialysis | Follow equipment manufacturer’s operating directions carefully.

- See full prescribing information for recommended pediatric dosage. (2.4)

3 DOSAGE FORMS AND STRENGTHS

Heparin sodium is available as: (3)

Heparin Sodium in 0.45% Sodium Chloride Injection:

- Injection: 50 USP units per mL in 0.45% Sodium Chloride clear solution (25,000 USP units per 500 mL) in single-dose freeflex® bag
- Injection: 100 USP units per mL in 0.45% Sodium Chloride clear solution (25,000 USP units per 250 mL) in single-dose freeflex® bag

Heparin Sodium in 5% Dextrose Injection:

- Injection: 50 USP units per mL in 5% Dextrose clear solution (25,000 USP units per 500 mL) in single-dose freeflex® bag
- Injection: 100 USP units per mL in 5% Dextrose clear solution (25,000 USP units per 250 mL) in single-dose freeflex® bag

4 CONTRAINDICATIONS

- History of Heparin-Induced Thrombocytopenia (HIT) and Heparin-Induced Thrombocytopenia and Thrombosis (HITT) (4)
- Known hypersensitivity to heparin or pork products (4)
- In whom suitable blood coagulation tests cannot be performed at appropriate intervals (4)

5 WARNINGS AND PRECAUTIONS

- Fatal Medication Errors: Confirm choice of correct strength prior to administration. (5.1)
- Hemorrhage: Fatal cases have occurred. Use caution in conditions with increased risk of hemorrhage. (5.2)
- HIT and HITT: Monitor for signs and symptoms and discontinue if indicative of HIT and HITT. (5.3)
- Monitoring: Blood coagulation tests guide therapy for full-dose heparin. Monitor platelet count and hematocrit in all patients receiving heparin. (5.5)

6 ADVERSE REACTIONS

Most common adverse reactions are hemorrhage, thrombocytopenia, HIT and HITT, hypersensitivity reactions, and elevations of aminotransferase levels. (6.1)

To report SUSPECTED ADVERSE REACTIONS, contact Fresenius Kabi USA, LLC at 1-800-551-7176 or FDA at 1-800-FDA-1088 or www.fda.gov/medwatch.

7 DRUG INTERACTIONS

Drugs that interfere with coagulation, platelet aggregation or drugs that counteract coagulation may induce bleeding. (7)

FULL PRESCRIBING INFORMATION

1 INDICATIONS AND USAGE

Heparin sodium is indicated for:

- Prophylaxis and treatment of venous thromboembolism and pulmonary embolism;
- Atrial fibrillation with embolization;
- Treatment of acute and chronic consumptive coagulopathies (disseminated intravascular coagulation);
- Prevention of clotting in arterial and cardiac surgery;
- Prophylaxis and treatment of peripheral arterial embolism;
- Anticoagulant use in blood transfusions, extracorporeal circulation, and dialysis procedures.

2 DOSAGE AND ADMINISTRATION

2.1 Preparation for Administration

Confirm the selection of the correct formulation and strength prior to administration of the drug.

INSTRUCTIONS FOR USE for the freeflex® Bag

Leave bag in the overwrap until time of use.

The intact port cap provides visual tamper evidence. Do not use if port cap is prematurely removed.

Maintain strict aseptic technique during handling.

To Open:

1. Always inspect the bag before and after removal from the overwrap.
2. Place the bag on a clean, flat surface. Starting in the bottom corner, peel the overwrap open and remove the bag.
3. Check the bag for leaks by squeezing firmly. If leaks are found, discard the bag.
4. Do not use if the solution is cloudy or a precipitate is present.

To Prepare for Administration:

1. Immediately before connecting the infusion set, firmly grasp the BLUE infusion port cap with the arrow pointing away from the bag between index finger and thumb. Gently break off the port cap. The membrane of the infusion port is sterile, and disinfection before initial use is not necessary if proper aseptic handling technique is followed.
2. Use a non-vented infusion set or close the air-inlet on a vented set. The BLUE infusion port is compatible with spike systems produced according to ISO 8536-4, with an external spike diameter of 5.5 to 5.7 mm.
3. Close the roller clamp of the infusion set.
4. Hold the base of the BLUE infusion port and insert the spike by rotating your wrist slightly until the spike is fully inserted.
5. The port membrane contains a self-sealing septum that helps prevent leakage after removing the spike. The infusion port is not intended to be spiked more than once.
6. Hang from the hole at the top of the bag.
7. For Single Use Only. Discard unused portion.

Do not admix with other drugs.

Do not use flexible container in series connections.

Parenteral drug products should be inspected visually for particulate matter and discoloration prior to administration, whenever solution and container permit.

2.2 Laboratory Monitoring for Efficacy and Safety

Adjust the dosage of heparin sodium according to the patient’s coagulation test results. When heparin is given by continuous intravenous infusion, determine the coagulation time approximately every 4 hours in the early stages of treatment. When the drug is administered intermittently by intravenous injection, perform coagulation tests before each injection during the early stages of treatment and at appropriate intervals thereafter. Dosage is considered adequate when the activated partial thromboplastin time (APTT) is 1.5 to 2 times the normal or when the whole blood clotting time is elevated approximately 2.5 to 3 times the control value.

Periodic platelet counts, hematocrits, and tests for occult blood in stool are recommended during the entire course of heparin therapy.

2.3 Therapeutic Anticoagulant Effect with Full-Dose Heparin

The dosing recommendations in Table 1 are based on clinical experience. Although dosage must be adjusted for the individual patient according to the results of suitable laboratory tests, the following dosage schedules may be used as guidelines:

Table 1: Recommended Adult Full-Dose Heparin Regimens for Therapeutic Anticoagulant Effect

Method of Administration | Frequency | Recommended Dose*
Intermittent Intravenous Injection | Initial Dose | 10,000 units
Intermittent Intravenous Injection | Every 4 to 6 hours | 5,000 to 10,000 units
Continuous Intravenous Infusion | Initial Dose | 5,000 units by intravenous injection
Continuous Intravenous Infusion | Continuous | 20,000 to 40,000 units per 24 hours

* Based on 150 lb. (68 kg) patient.

2.4 Pediatric Use

There are no adequate and well-controlled studies on heparin use in pediatric patients. Pediatric dosing recommendations are based on clinical experience. In general, the following dosage schedule may be used as a guideline in pediatric patients:

Initial Dose: 75 to 100 units/kg (intravenous bolus over 10 minutes)
Maintenance Dose Infants: 25 to 30 units/kg/hour;
Infants < 2 months have the highest requirements (average 28 units/kg/hour)
Children > 1 year of age: 18 to 20 units/kg/hour;
Older children may require less heparin, similar to weight-adjusted adult dosage
Monitoring: Adjust heparin to maintain aPTT of 60 to 85 seconds, assuming this reflects an
anti-Factor Xa level of 0.35 to 0.70.

2.5 Cardiovascular Surgery

Patients undergoing total body perfusion for open-heart surgery should receive an initial dose of not less than 150 units of heparin sodium per kilogram of body weight. Frequently, a dose of 300 units per kilogram is used for procedures estimated to last less than 60 minutes or 400 units per kilogram for those estimated to last longer than 60 minutes.

2.6 Converting to Warfarin

To ensure continuous anticoagulation when converting from Heparin Sodium to warfarin, continue full heparin therapy for several days until the INR (prothrombin time) has reached a stable therapeutic range. Heparin therapy may then be discontinued without tapering [see Drug Interactions (7.1)].

2.7 Converting to Oral Anticoagulants other than Warfarin

For patients currently receiving intravenous heparin, stop intravenous infusion of heparin sodium immediately after administering the first dose of oral anticoagulant; or for intermittent intravenous administration of heparin sodium, start oral anticoagulant 0 to 2 hours before the time that the next dose of heparin was to have been administered.

2.8 Extracorporeal Dialysis

Follow equipment manufacturer’s operating directions carefully. A dose of 25 to 30 units/kg followed by an infusion rate of 1,500 to 2,000 units/hour is suggested based on pharmacodynamic data if specific manufacturers' recommendations are not available.

3 DOSAGE FORMS AND STRENGTHS

Heparin Sodium in 0.45% Sodium Chloride Injection is available as:

- Injection: 50 USP units per mL in 0.45% Sodium Chloride clear solution (25,000 USP units per 500 mL) in single-dose freeflex® bag
- Injection: 100 USP units per mL in 0.45% Sodium Chloride clear solution (25,000 USP units per 250 mL) in single-dose freeflex® bag

Heparin Sodium in 5% Dextrose Injection is available as:

- Injection: 50 USP units per mL in 5% Dextrose clear solution (25,000 USP units per 500 mL) in single-dose freeflex® bag
- Injection: 100 USP units per mL in 5% Dextrose clear solution (25,000 USP units per 250 mL) in single-dose freeflex® bag

4 CONTRAINDICATIONS

The use of Heparin Sodium in 0.45% Sodium Chloride Injection or Heparin Sodium in 5% Dextrose Injection is contraindicated in patients with the following conditions:

- History of Heparin-Induced Thrombocytopenia (HIT) and Heparin-Induced Thrombocytopenia and Thrombosis (HITT) [see Warnings and Precautions (5.3)]
- Known hypersensitivity to heparin or pork products (e.g., anaphylactoid reactions) [see Adverse Reactions (6.1)]
- In whom suitable blood coagulation tests — e.g., the whole blood clotting time, partial thromboplastin time, etc., — cannot be performed at appropriate intervals (this contraindication refers to full-dose heparin; there is usually no need to monitor coagulation parameters in patients receiving low-dose heparin) [see Warnings and Precautions (5.5)]
- An uncontrolled bleeding state [see Warnings and Precautions (5.2)], except when this is due to disseminated intravascular coagulation.

5 WARNINGS AND PRECAUTIONS

5.1 Fatal Medication Errors

Do not use this product as a “catheter lock flush” product. Heparin is supplied in various strengths. Fatal hemorrhages have occurred due to medication errors. Carefully examine all heparin products to confirm the correct container choice prior to administration of the drug.

5.2 Hemorrhage

Avoid using heparin in the presence of major bleeding, except when the benefits of heparin therapy outweigh the potential risks.

Hemorrhage, including fatal events, has occurred in patients receiving Heparin Sodium. Hemorrhage can occur at virtually any site in patients receiving heparin. Adrenal hemorrhage (with resultant acute adrenal insufficiency), ovarian hemorrhage, and retroperitoneal hemorrhage have occurred during anticoagulant therapy with heparin [see Adverse Reactions (6.1)]. A higher incidence of bleeding has been reported in patients, particularly women, over 60 years of age [see Clinical Pharmacology (12.3)]. An unexplained fall in hematocrit or fall in blood pressure should lead to serious consideration of a hemorrhagic event.

Use heparin sodium with caution in disease states in which there is increased risk of hemorrhage, including:

- Cardiovascular — Subacute bacterial endocarditis, severe hypertension.
- Surgical — During and immediately following (a) spinal tap or spinal anesthesia or (b) major surgery, especially involving the brain, spinal cord or eye.
- Hematologic — Conditions associated with increased bleeding tendencies, such as hemophilia, thrombocytopenia and some vascular purpuras.
- Patients with hereditary antithrombin III deficiency receiving concurrent antithrombin III therapy — The anticoagulant effect of heparin is enhanced by concurrent treatment with antithrombin III (human) in patients with hereditary antithrombin III deficiency. To reduce the risk of bleeding, reduce the heparin dose during concomitant treatment with antithrombin III (human).
- Gastrointestinal — Ulcerative lesions and continuous tube drainage of the stomach or small intestine.
- Other — Menstruation, liver disease with impaired hemostasis.

5.3 Heparin-Induced Thrombocytopenia (HIT) and Heparin-Induced Thrombocytopenia and Thrombosis (HITT)

HIT is a serious antibody-mediated reaction resulting from irreversible aggregation of platelets. HIT occurs in patients treated with heparin and is due to the development of antibodies to a platelet Factor 4-heparin complex that induce in vivo platelet aggregation. HIT may progress to the development of venous and arterial thromboses, a condition known as heparin-induced thrombocytopenia and thrombosis (HITT). Thrombotic events may also be the initial presentation for HITT. These serious thromboembolic events include deep vein thrombosis, pulmonary embolism, cerebral vein thrombosis, limb ischemia, stroke, myocardial infarction, thrombus formation on a prosthetic cardiac valve, mesenteric thrombosis, renal arterial thrombosis, skin necrosis, gangrene of the extremities that may lead to amputation, and possibly death. Monitor thrombocytopenia of any degree closely. If the platelet count falls below 100,000/mm^3 or if recurrent thrombosis develops, promptly discontinue heparin, evaluate for HIT and HITT, and, if necessary, administer an alternative anticoagulant.
HIT or HITT can occur up to several weeks after the discontinuation of heparin therapy. Patients presenting with thrombocytopenia or thrombosis after discontinuation of heparin should be evaluated for HIT or HITT.

5.4 Thrombocytopenia

Thrombocytopenia has been reported to occur in patients receiving heparin with a reported incidence of up to 30%. It can occur 2 to 20 days (average 5 to 9) following the onset of heparin therapy. Obtain platelet counts before and periodically during heparin therapy. Monitor thrombocytopenia of any degree closely. If the count falls below 100,000/mm^3 or if recurrent thrombosis develops, promptly discontinue heparin, evaluate for HIT and, if necessary, administer an alternative anticoagulant [see Warnings and Precautions (5.3)].

5.5 Coagulation Testing and Monitoring

When using a full dose heparin regimen, adjust the heparin dose based on frequent blood coagulation tests. If the coagulation test is unduly prolonged or if hemorrhage occurs, heparin sodium should be discontinued promptly [see Overdosage (10)]. Periodic platelet counts, hematocrits are recommended during the entire course of heparin therapy [see Dosage and Administration (2.2)].

5.6 Heparin Resistance

Increased resistance to heparin is frequently encountered in fever, thrombosis, thrombophlebitis, infections with thrombosing tendencies, myocardial infarction, cancer, in postsurgical patients, and patients with antithrombin III deficiency. Close monitoring of coagulation tests is recommended in these cases. Adjustment of heparin doses based on anti-Factor Xa levels may be warranted.

5.7 Hypersensitivity

Patients with documented hypersensitivity to heparin should be given the drug only in clearly life-threatening situations [see Adverse Reactions (6.1)]. Because heparin sodium is derived from animal tissue, monitor for signs and symptoms of hypersensitivity when it is used in patients with a history of allergy.

Heparin Sodium in 5% Dextrose Injection

This product contains sodium metabisulfite, a sulfite that may cause allergic-type reactions including anaphylactic symptoms and life-threatening or less severe asthmatic episodes in certain susceptible people. The overall prevalence of sulfite sensitivity in the general population is unknown and probably low. Sulfite sensitivity is seen more frequently in asthmatic than in nonasthmatic people.

6 ADVERSE REACTIONS

The following serious adverse reactions are described elsewhere in the labeling:

- Hemorrhage [see Warnings and Precautions (5.2)]
- Heparin-Induced Thrombocytopenia (HIT) and Heparin-Induced Thrombocytopenia and Thrombosis (HITT) [see Warnings and Precautions (5.3)]
- Thrombocytopenia [see Warnings and Precautions (5.4)]
- Heparin Resistance [see Warnings and Precautions (5.6)]
- Hypersensitivity [see Warnings and Precautions (5.7)]

6.1 Postmarketing Experience

The following adverse reactions have been identified during post-approval use of heparin sodium. Because these reactions are reported voluntarily from a population of uncertain size, it is not always possible to reliably estimate their frequency.

- Hemorrhage – Hemorrhage is the chief complication that may result from heparin therapy [see Warnings and Precautions (5.2)]. Gastrointestinal or urinary tract bleeding during anticoagulant therapy may indicate the presence of an underlying occult lesion. Bleeding can occur at any site but certain specific hemorrhagic complications may be difficult to detect:

– Adrenal hemorrhage, with resultant acute adrenal insufficiency, has occurred with
heparin therapy, including fatal cases.
– Ovarian (corpus luteum) hemorrhage developed
in a number of women of reproductive age receiving short- or long-term anticoagulant
therapy.

– Retroperitoneal hemorrhage.

- HIT and HITT, including delayed onset cases [see Warnings and Precautions (5.3 and 5.4)].
- Hypersensitivity – Generalized hypersensitivity reactions have been reported with chills, fever, and urticaria as the most usual manifestations, and asthma, rhinitis, lacrimation, headache, nausea and vomiting, and anaphylactoid reactions, including shock, occurring more rarely. Itching and burning, especially on the plantar side of the feet, may occur [see Warnings and Precautions (5.7)].
- Elevations of serum aminotransferases – Significant elevations of aspartate aminotransferase (AST) and alanine aminotransferase (ALT) levels have occurred in patients who have received heparin.
- Others– Osteoporosis following long-term administration of high-doses of heparin, cutaneous necrosis after systemic administration, suppression of aldosterone synthesis, delayed transient alopecia, priapism, and rebound hyperlipemia on discontinuation of heparin sodium have also been reported.

7 DRUG INTERACTIONS

7.1 Oral Anticoagulants

Heparin sodium may prolong the one-stage prothrombin time. Therefore, when heparin sodium is given with dicumarol or warfarin sodium, a period of at least 5 hours after the last intravenous dose or 24 hours after the last subcutaneous dose should elapse before blood is drawn if a valid prothrombin time is to be obtained.

7.2 Platelet Inhibitors

Drugs such as NSAIDS (including salicylic acid, ibuprofen, indomethacin, and celecoxib), dextran, phenylbutazone, thienopyridines, dipyridamole, hydroxychloroquine, glycoprotein IIb/IIIa antagonists (including abciximab, eptifibatide, and tirofiban), and others that interfere with platelet-aggregation reactions (the main hemostatic defense of heparinized patients) may induce bleeding and should be used with caution in patients receiving heparin sodium. To reduce the risk of bleeding, a reduction in the dose of antiplatelet agent or heparin is recommended.

7.3 Other Interactions

Digitalis, tetracyclines, nicotine, antihistamines, or intravenous nitroglycerin may partially counteract the anticoagulant action of heparin sodium.

Heparin Sodium in 5% Dextrose Injection

Intravenous nitroglycerin administered to heparinized patients may result in a decrease of the partial thromboplastin time with subsequent rebound effect upon discontinuation of nitroglycerin. Careful monitoring of partial thromboplastin time and adjustment of heparin dosage are recommended during coadministration of heparin and intravenous nitroglycerin.

Antithrombin III (human) – The anticoagulant effect of heparin is enhanced by concurrent treatment with antithrombin III (human) in patients with hereditary antithrombin III deficiency. To reduce the risk of bleeding, a reduced dosage of heparin is recommended during treatment with antithrombin III (human).

8 USE IN SPECIFIC POPULATIONS

8.1 Pregnancy

Risk Summary
There are no available data on heparin sodium use in pregnant women to inform a drug-associated risk of major birth defects and miscarriage. In published reports, heparin exposure during pregnancy did not show evidence of an increased risk of adverse maternal or fetal outcomes in humans. No teratogenicity, but early embryo-fetal death was observed in animal reproduction studies with administration of heparin sodium to pregnant rats and rabbits during organogenesis at doses approximately 10 times the maximum recommended human dose (MRHD) of 40,000 units/24 hours infusion (see Data). Consider the benefits and risks of Heparin Sodium in 0.45% Sodium Chloride Injection or Heparin Sodium in 5% Dextrose Injection to a pregnant woman and possible risks to the fetus when prescribing Heparin Sodium in 0.45% Sodium Chloride Injection or Heparin Sodium in 5% Dextrose Injection to a pregnant woman.
The estimated background risk of major birth defects and miscarriage for the indicated population is unknown. All pregnancies have a background risk of birth defect, loss, or other adverse outcomes. In the U.S. general population, the estimated background risk of major birth defects and miscarriage in clinically recognized pregnancies is 2 to 4% and 15 to 20%, respectively.
Data
Human Data
The maternal and fetal outcomes associated with uses of heparin via various dosing methods and administration routes during pregnancy have been investigated in numerous studies. These studies generally reported normal deliveries with no maternal or fetal bleeding and no other complications.
Animal Data
In a published study conducted in rats and rabbits, pregnant animals received heparin intravenously during organogenesis at a dose of 10,000 USP units/kg/day, approximately 10 times the maximum human daily dose based on body weight. The number of early resorptions increased in both species. There was no evidence of teratogenic effects.

8.2 Lactation

Risk Summary

There is no information regarding the presence of Heparin Sodium in 0.45% Sodium Chloride Injection or Heparin Sodium in 5% Dextrose Injection in human milk, the effects on the breastfed infant, or the effects on milk production. Due to its large molecular weight, heparin is not likely to be excreted in human milk, and any heparin in milk would not be orally absorbed by a nursing infant. The developmental and health benefits of breastfeeding should be considered along with the mother’s clinical need for Heparin Sodium in 0.45% Sodium Chloride Injection or Heparin Sodium in 5% Dextrose Injection and any potential adverse effects on the breastfed infant from Heparin Sodium in 0.45% Sodium Chloride Injection or Heparin Sodium in 5% Dextrose Injection or from the underlying maternal condition [see Use in Specific Populations (8.4)].

8.4 Pediatric Use

There are no adequate and well-controlled studies on heparin use in pediatric patients. Pediatric dosing recommendations are based on clinical experience [see Dosage and Administration (2.4)].

8.5 Geriatric Use

There are limited adequate and well-controlled studies in patients 65 years and older. However, a higher incidence of bleeding has been reported in patients over 60 years of age, especially women [see Warnings and Precautions (5.2)]. Lower doses of heparin may be indicated in these patients [see Clinical Pharmacology (12.3)].

10 OVERDOSAGE

Bleeding may result from heparin overdosage.

Neutralization of heparin effect

When circumstances (e.g., bleeding) require reversal of heparinization, protamine sulfate (1% solution) by slow infusion will neutralize heparin sodium.

No more than 50 mg should be administered, very slowly, in any 10 minute period. Each mg of protamine sulfate neutralizes approximately 100 USP units. The amount of protamine required decreases over time as heparin is metabolized. Although the metabolism of heparin is complex, it may, for the purpose of choosing a protamine dose, be assumed to have a half-life of about 1/2 hour after intravenous injection.

Because fatal reactions often resembling anaphylaxis have been reported, the drug should be given only when resuscitation techniques and treatment of anaphylactoid shock are readily available.

For additional information, consult the prescribing information for Protamine Sulfate Injection, USP.

11 DESCRIPTION

Heparin is a heterogeneous group of straight-chain anionic mucopolysaccharides, called glycosaminoglycans, possessing anticoagulant properties. It is composed of polymers of alternating derivations of α-D-glucosamido (N-sulfated O-sulfated O-sulfated or N-acetylated) and O-sulfated uronic acid (α-L-iduronic acid or β-D-glucoronic acid).

Structure of Heparin Sodium (representative subunits):

Heparin Sodium in 0.45% Sodium Chloride Injection and Heparin Sodium in 5% Dextrose Injection are sterile, nonpyrogenic solutions prepared from heparin sodium (derived from porcine intestinal mucosa) for intravenous administration. The potency is determined by a biological assay using a USP reference standard based on units of heparin activity per milligram.

Heparin Sodium in 0.45% Sodium Chloride Injection, is available as follows:

Each 100 mL contains heparin sodium 5,000 or 10,000 USP Units; sodium chloride, 0.45 g; edetate disodium, dihydrate, 0.0111 g added as a stabilizer and water for injection, q.s. Each liter contains the following electrolytes: Sodium 77 mEq and chloride 77 mEq; pH 5.0 to 7.5. The solution may contain sodium hydroxide and/or hydrochloric acid for pH adjustment.

Heparin Sodium in 5% Dextrose Injection, is available as follows:

Each 100 mL contains heparin sodium 5,000 or 10,000 USP Units; dextrose hydrous, 5 g; citric acid anhydrous, 51 mg and sodium citrate dihydrate, 334 mg added as buffers; and sodium metabisulfite, 20 mg added as an antioxidant. Each liter contains the following electrolytes: Sodium 39 mEq and citrate 42 mEq; pH 5.0 to 7.5.

12 CLINICAL PHARMACOLOGY

12.1 Mechanism of Action

Heparin interacts with the naturally occurring plasma protein, Antithrombin III, to induce a conformational change, which markedly enhances the serine protease activity of Antithrombin III, thereby inhibiting the activated coagulation factors involved in the clotting sequence, particularly Xa and IIa. Small amounts of heparin inhibit Factor Xa, and larger amounts inhibit thrombin (Factor IIa). Heparin also prevents the formation of a stable fibrin clot by inhibiting the activation of the fibrin stabilizing factor. Heparin does not have fibrinolytic activity; therefore, it will not lyse existing clots.

12.2 Pharmacodynamics

Bleeding time is usually unaffected by heparin. Various times (activated clotting time, activated partial thromboplastin time, prothrombin time, whole blood clotting time) are prolonged by full therapeutic doses of heparin; in most cases it is not measurably affected by low doses of heparin.

12.3 Pharmacokinetics

Absorption
Heparin is not absorbed through the gastrointestinal tract and therefore administered via parenteral route. Peak plasma concentration and the onset of action are achieved immediately after intravenous administration.
Distribution
Heparin is highly bound to antithrombin, fibrinogens, globulins, serum proteases and lipoproteins. The volume of distribution is 0.07 L/kg.
Elimination
Metabolism
Heparin does not undergo enzymatic degradation.
Excretion
Heparin is mainly cleared from the circulation by liver and reticuloendothelial cells mediated uptake into extravascular space. Heparin undergoes biphasic clearance, a) rapid saturable clearance (zero order process due to binding to proteins, endothelial cells and macrophage) and b) slower first order elimination. The plasma half-life is dose-dependent and it ranges from 0.5 to 2 h.
Specific Population
Geriatric patients
Patients over 60 years of age, following similar doses of heparin, may have higher plasma levels of heparin and longer activated partial thromboplastin times (APTTs) compared with patients under 60 years of age [see Use in Specific Populations (8.5)].

13 NONCLINICAL TOXICOLOGY

13.1 Carcinogenesis, Mutagenesis, Impairment of Fertility

No long-term studies in animals have been performed to evaluate the carcinogenic potential of heparin. Also, no studies in animals have been performed concerning mutagenesis or impairment of fertility.

16 HOW SUPPLIED/STORAGE AND HANDLING

Heparin Sodium in 0.45% Sodium Chloride Injection is supplied as follows:

Product Code | Unit of Sale | Strength | Each
518077 | NDC 63323-518-77 Unit of 24 | 25,000 USP units per 500 mL (50 USP units per mL) | NDC 63323-518-01 500 mL Single Dose freeflex® Bag
517074 | NDC 63323-517-74 Unit of 24 | 25,000 USP units per 250 mL (100 USP units per mL) | NDC 63323-517-01 250 mL Single Dose freeflex® Bag

Heparin Sodium in 5% Dextrose Injection is supplied as follows:

Product Code | Unit of Sale | Strength | Each
507277 | NDC 63323-522-77 Unit of 24 | 25,000 USP units per 500 mL (50 USP units per mL) | NDC 63323-522-01 500 mL Single Dose freeflex® Bag
507374 | NDC 63323-523-74 Unit of 24 | 25,000 USP units per 250 mL (100 USP units per mL) | NDC 63323-523-01 250 mL Single Dose freeflex® Bag

Store at 20° to 25°C (68° to 77°F) [see USP Controlled Room Temperature]. Avoid excessive heat.
Do not freeze.

The container closure is not made with natural rubber latex.

Non-PVC, Non-DEHP, Sterile.

17 PATIENT COUNSELING INFORMATION

Hemorrhage

Inform patients that it may take them longer than usual to stop bleeding, that they may bruise and/or bleed more easily when they are treated with heparin, and that they should report any unusual bleeding or bruising to their physician. Hemorrhage can occur at virtually any site in patients receiving heparin. Fatal hemorrhages have occurred [see Warnings and Precautions (5.2)].

Prior to Surgery

Advise patients to inform physicians and dentists that they are receiving heparin before any surgery is scheduled [see Warnings and Precautions (5.2)].

Heparin-Induced Thrombocytopenia

Inform patients of the risk of heparin-induced thrombocytopenia (HIT). HIT may progress to the development of venous and arterial thromboses, a condition known as heparin-induced thrombocytopenia and thrombosis. HIT and HITT can occur up to several weeks after the discontinuation of heparin therapy [see Warnings and Precautions (5.3 and 5.4)].

Hypersensitivity

Inform patients that generalized hypersensitivity reactions have been reported [see Warnings and Precautions (5.7), Adverse Reactions (6)].

Other Medications

Because of the risk of hemorrhage, advise patients to inform their physicians and dentists of all medications they are taking, including non-prescription medications, and before starting any new medication [see Drug Interactions (7.2)].
Manufactured for:
Made in Norway
www.fresenius-kabi.com/us
451475C
Revised: December 2019

PACKAGE LABEL

PACKAGE LABEL - PRINCIPAL DISPLAY PANEL - Heparin Sodium 500 mL Bag Label

NDC 63323-518-01

Heparin
Heparin Sodium in 0.45% Sodium Chloride Injection
25,000 USP units per 500 mL (50 USP units per mL)
For intravenous use only.
Single Dose Container.
Discard unused portion.
Rx only
DO NOT ADMIX WITH OTHER DRUGS.

PACKAGE LABEL

PACKAGE LABEL - PRINCIPAL DISPLAY PANEL - Heparin 500 mL Bag Shipper Label

Product No. 518077

Heparin

Heparin Sodium in 0.45% Sodium Chloride Injection

25,000 USP units

per 500 mL

(50 USP units per mL)

NDC 63323-518-77

Rx only

PACKAGE LABEL

PACKAGE LABEL - PRINCIPAL DISPLAY PANEL - Heparin Sodium 250 mL Bag Label

NDC 63323-517-01

Heparin
Heparin Sodium in 0.45% Sodium Chloride Injection
25,000 USP units per 250 mL (100 USP units per mL)
For intravenous use only.
Rx only
Single Dose Container.
Discard unused portion.
DO NOT ADMIX WITH OTHER DRUGS.

PACKAGE LABEL

PACKAGE LABEL - PRINCIPAL DISPLAY PANEL - Heparin 250 mL Bag Shipper Label

Product No. 517074

Heparin

Heparin Sodium in 0.45% Sodium Chloride Injection

25,000 USP units

per 250 mL

(100 USP units per mL)

NDC 63323-517-74

Rx only

PACKAGE LABEL

PACKAGE LABEL - PRINCIPAL DISPLAY PANEL - Heparin Sodium 500 mL Bag Label

NDC 63323-522-01

Heparin
Heparin Sodium in 5% Dextrose Injection
25,000 USP units per 500 mL (50 USP units per mL)
For intravenous use only.
Single Dose Container.
Discard unused portion.
Rx only
CONTAINS SULFITES. DO NOT ADMIX WITH OTHER DRUGS.

PACKAGE LABEL

PACKAGE LABEL - PRINCIPAL DISPLAY PANEL - Heparin 500 mL Bag Shipper Label

Product No. 507277

Heparin

Heparin Sodium in 5% Dextrose Injection

25,000 USP units

per 500 mL

(50 USP units per mL)

NDC 63323-522-77

Rx only

PACKAGE LABEL

PACKAGE LABEL - PRINCIPAL DISPLAY PANEL - Heparin Sodium 250 mL Bag Label

NDC 63323-523-01

Heparin
Heparin Sodium in 5% Dextrose Injection
25,000 USP units per 250 mL (100 USP units per mL)
For intravenous use only.
Rx only
Single Dose Container.
Discard unused portion.
CONTAINS SULFITES. DO NOT ADMIX WITH OTHER DRUGS.

PACKAGE LABEL

PACKAGE LABEL - PRINCIPAL DISPLAY PANEL - Heparin 250 mL Bag Shipper Label

Product No. 507374

Heparin

Heparin Sodium in 5% Dextrose Injection

25,000 USP units

per 250 mL

(100 USP units per mL)

NDC 63323-523-74

Rx only